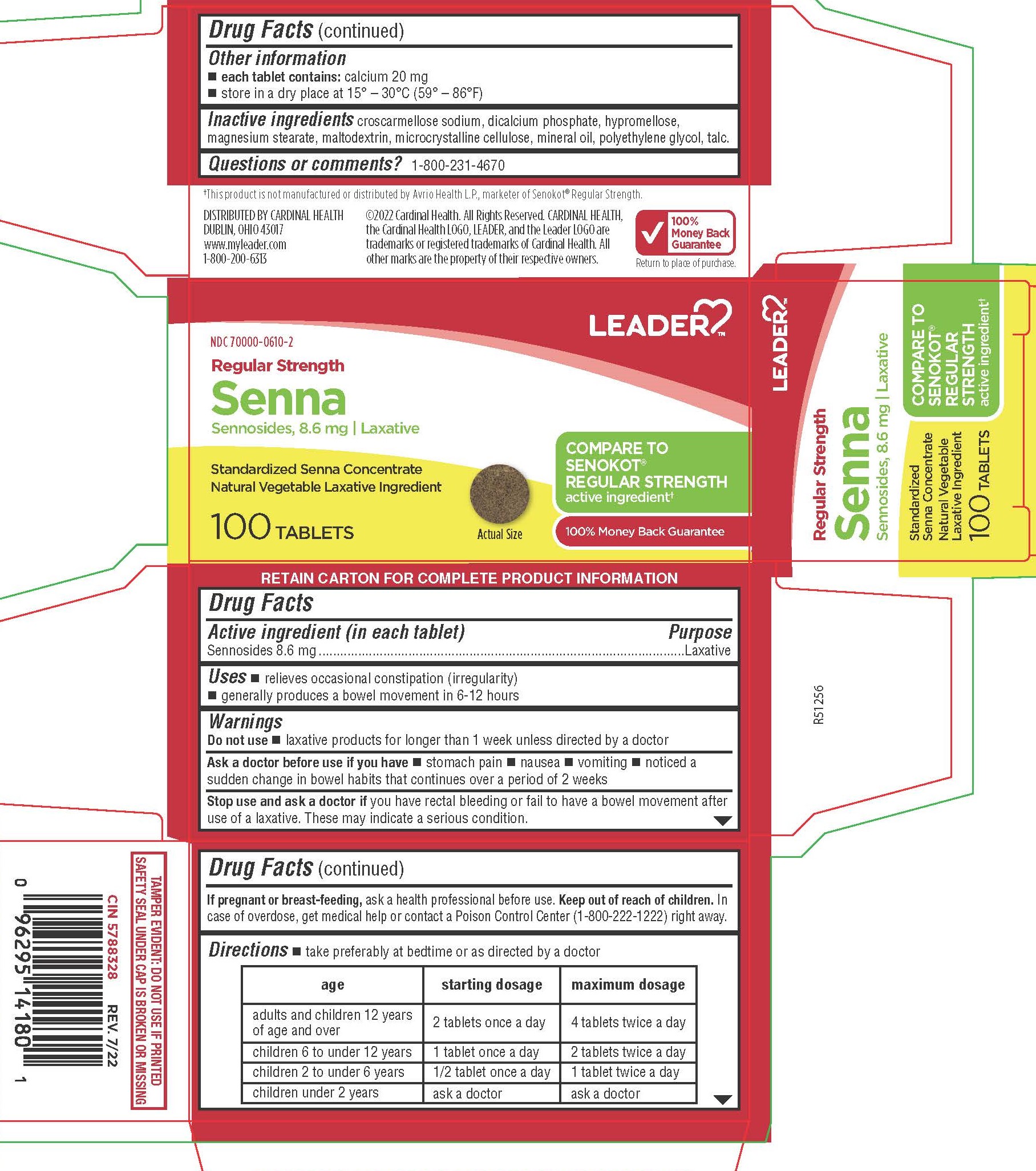 DRUG LABEL: Sennosides
NDC: 70000-0610 | Form: TABLET, FILM COATED
Manufacturer: LEADER/ Cardinal Health 110, Inc.
Category: otc | Type: HUMAN OTC DRUG LABEL
Date: 20250211

ACTIVE INGREDIENTS: SENNOSIDES 8.6 mg/1 1
INACTIVE INGREDIENTS: MAGNESIUM STEARATE; DIBASIC CALCIUM PHOSPHATE DIHYDRATE; CROSCARMELLOSE SODIUM; MALTODEXTRIN; HYPROMELLOSES; TALC; LIGHT MINERAL OIL; MICROCRYSTALLINE CELLULOSE; POLYETHYLENE GLYCOL 400

1122W - Cardinal

Drug Facts

Active ingredient (in each tablet)
Sennosides 8.6 mg

Purpose
Laxative

Uses

 relieves occasional constipation (irregularity)
 generally produces a bowel movement in 6-12 hours

WARNINGS

Do not use

 laxative products for longer than 1 week unless directed by a doctor

Ask a doctor before use if you have

 stomach pain

 nausea

 vomiting

 noticed a sudden change in bowel habits that continues over a period of 2 weeks

Stop use and ask a doctor if you have rectal bleeding or fail to have a bowel movement after use of a laxative. These may indicate a serious condition.

PREGNANCY OR BREAST FEEDING

If pregnant or breast-feeding, ask a health professional before use.

Keep out of reach of children.

OVERDOSAGE

In case of overdose, get medical help or contact a Poison Control Center (1-800-222-1222) right away.

Directions

 take preferably at bedtime or as directed by a doctor

age | starting dosage | maximum dosage
adults and children 12 years of age and over | 2 tablets once a day | 4 tablets twice a day
children 6 to under 12 years | 1 tablet once a day | 2 tablets twice a day
children 2 to under 6 years | 1/2 tablet once a day | 1 tablet twice a day
children under 2 years | ask a doctor | ask a doctor

Other information

 each tablet contains: calcium 20 mg
 store in a dry place at 15° – 30°C (59° – 86°F)

INACTIVE INGREDIENT

croscarmellose sodium, dicalcium phosphate, hypromellose, magnesium stearate, maltodextrin, microcrystalline cellulose, mineral oil, polyethylene glycol, talc.

Questions or comments?

1-800-231-4670

†This product is not manufactured or distributed by Avrio Health L.P., marketer of Senokot® Regular Strength.

DISTRIBUTED BY CARDINAL HEALTH
DUBLIN, OHIO 43017
www.myleader.com
1-800-200-6313

RETAIN CARTON FOR COMPLETE PRODUCT INFORMATION

TAMPER EVIDENT: DO NOT USE IF PRINTED SAFETY SEAL UNDER CAP IS BROKEN OR MISSING

PACKAGE LABEL

NDC 70000-0610-2

Regular Strength

Senna Sennosides, 8.6 mg | Laxative
Standardized Senna Concentrate
Natural Vegetable Laxative Ingredient

COMPARE TO SENOKOT® REGULAR STRENGTH active ingredient†

100 Tablets